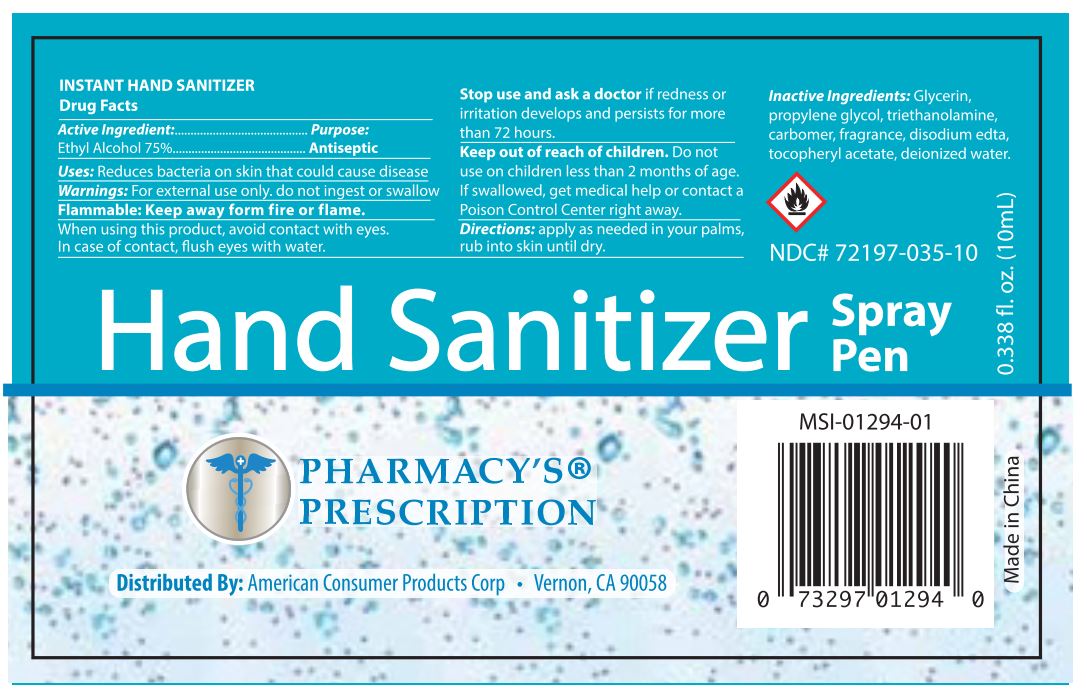 DRUG LABEL: PHARMACYS PRESCRIPTION HAND SANITIZER
NDC: 72197-035 | Form: LIQUID
Manufacturer: American Consumer Products Corp
Category: otc | Type: HUMAN OTC DRUG LABEL
Date: 20210715

ACTIVE INGREDIENTS: ALCOHOL 75 mL/100 mL
INACTIVE INGREDIENTS: .ALPHA.-TOCOPHEROL ACETATE; WATER; GLYCERIN; PROPYLENE GLYCOL 2-(2-METHYLBUTYRATE); CARBOMER HOMOPOLYMER TYPE C; TRIETHANOLAMINE 2-CYCLOHEXYL-4,6-DINITROPHENOLATE; EDETATE DISODIUM

Pharmacy's Prescription Hand Sanitizer

Active Ingredient

Active Ingredients: Ethyl Alcohol 75%

Purpose

Purpose: Antiseptic

Uses - Reduces bacteria on skin that could cause disease.

Warnings

Warnings - For external use only. Do not ingest or swallow.

Flammable. Keep away from fire or flame.

Stop Use

Stop use and ask a doctor if: If redness or irritation develops and persists for more than 72 hours.

Keep out of reach of children. Do not use on children less than 2 months of age. If swallowed, get medical help or contact a Poison Control Center right away.

Inactive Ingredients

Inactive ingredients - Glycerin, propylene glycol, triethanolamine, carbomer, fragrance, disodium edta, tocopheryl acetate, deionized water.

Directions

Directions: apply as needed in your palms, rub into skin until dry.

Indications & Usage Section

When using this product, avoid contact with eyes. In case of contact, flush eyes with water.